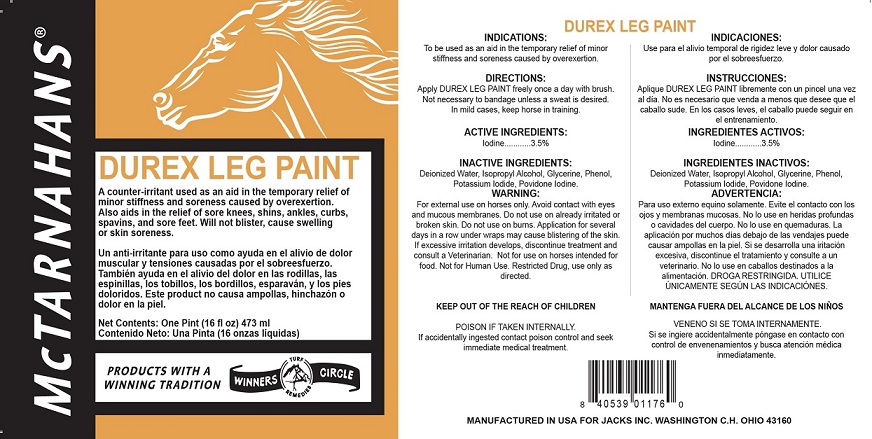 DRUG LABEL: DUREX LEG PAINT
NDC: 61156-111 | Form: LINIMENT
Manufacturer: JACKS MFG INC
Category: animal | Type: OTC ANIMAL DRUG LABEL
Date: 20211208

ACTIVE INGREDIENTS: IODINE 0.035 g/1 mL
INACTIVE INGREDIENTS: POTASSIUM IODIDE 0.0251 g/1 mL; ISOPROPYL ALCOHOL 0.36 mL/1 mL; GLYCERIN 0.3 g/1 mL; PHENOL 0.0258 mL/1 mL; WATER 0.366 mL/1 mL; POVIDONE 0.019 g/1 mL

DUREX LEG PAINT

INDICATIONS

To be used as an aid in the temporary relief of minor stiffness and soreness caused by overexertion.

Directions

Apply DUREX LEG PAINT freely once a day with brush.

Not necessary to bandage unless a sweat is desired.

In mild cases, keep horse in training.

WARNING

For external use on horses only.

Avoid contact with eyes and mucous membranes.

Do not use on already irritated or broken skin.

Do not use on burns.

Application for several days in a row under wraps may cause blistering of the skin.

If excessive irritation develops, discontinue treatment and consult a Veterinarian.

Not for use on horses intended for food.

Not for Human Use.

Restricted Drug, use only as directed

KEEP OUT OF THE REACH OF CHILDREN

POISON IF TAKEN INTERNALLY. If accidentally ingested contact poison control and seek immediate medical treatment.